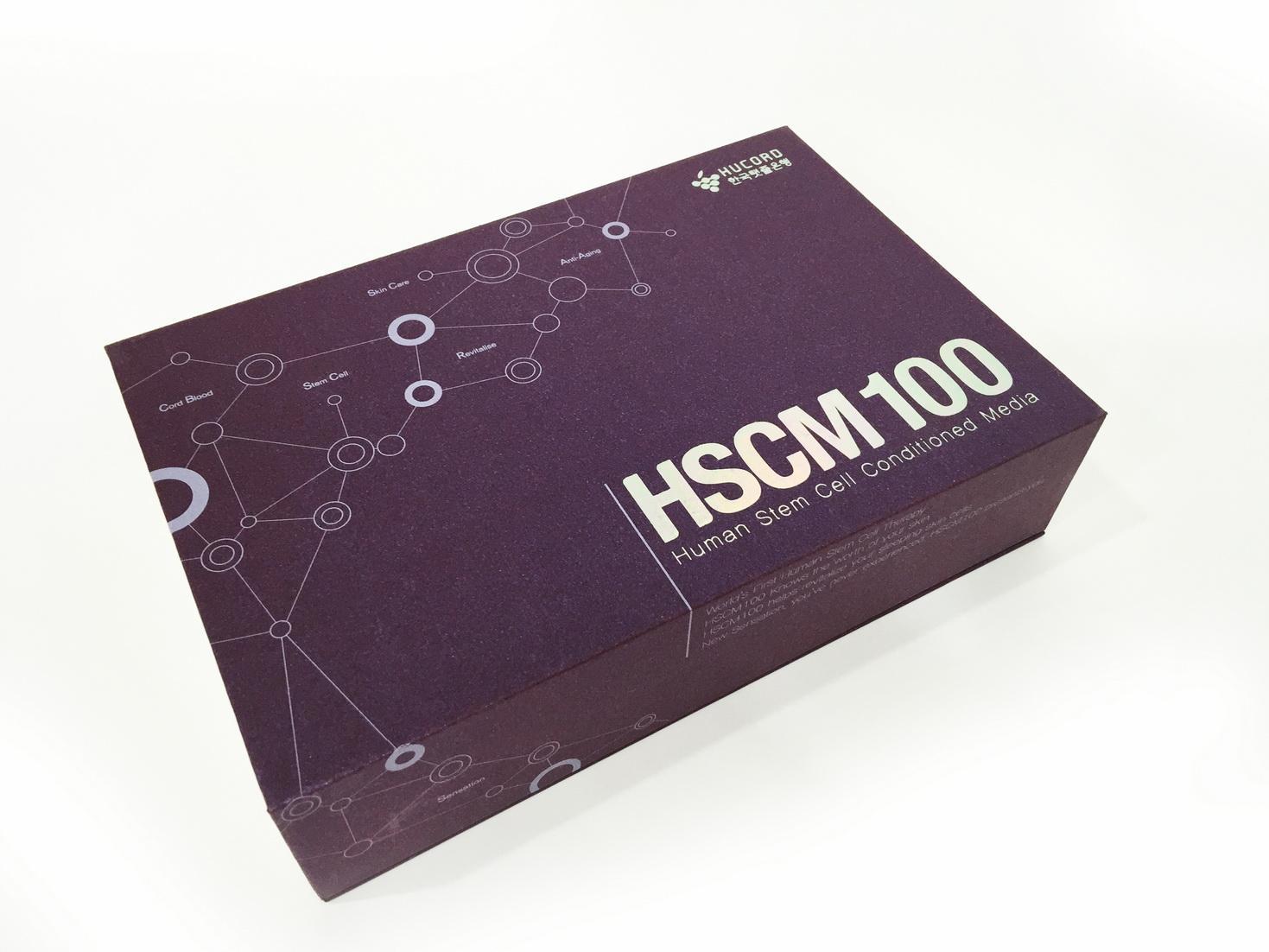 DRUG LABEL: HUCORD HSCM-100 Ampoule
NDC: 70373-0003 | Form: LIQUID
Manufacturer: Hucord Co., Ltd.
Category: otc | Type: HUMAN OTC DRUG LABEL
Date: 20191223

ACTIVE INGREDIENTS: INSULIN-LIKE GROWTH FACTOR-2 0.0000633 g/100 mL
INACTIVE INGREDIENTS: INTERLEUKIN-8; HUMAN EPIDERMAL GROWTH FACTOR

Drug Facts

ACTIVE INGREDIENT

dimethicone

INACTIVE INGREDIENT

water, butylene glycol, etc.

PURPOSE

anti aging

KEEP OUT OF REACH OF CHILDREN

keep out of reach of the children

INDICATIONS & USAGE

apply proper amount to the skin

WARNINGS

1. Do not use in the following cases(Eczema and scalp wounds)
2.Side Effects
1)Due to the use of this druf if rash, irritation, itching and symptopms of hypersnesitivity occur dicontinue use and consult your phamacisr or doctor
3.General Precautions
1)If in contact with the eyes, wash out thoroughty with water If the symptoms are servere, seek medical advice immediately
2)This product is for exeternal use only. Do not use for internal use
4.Storage and handling precautions
1)If possible, avoid direct sunlight and store in cool and area of low humidity
2)In order to maintain the quality of the product and avoid misuse
3)Avoid placing the product near fire and store out in reach of children

DOSAGE & ADMINISTRATION

for external use only